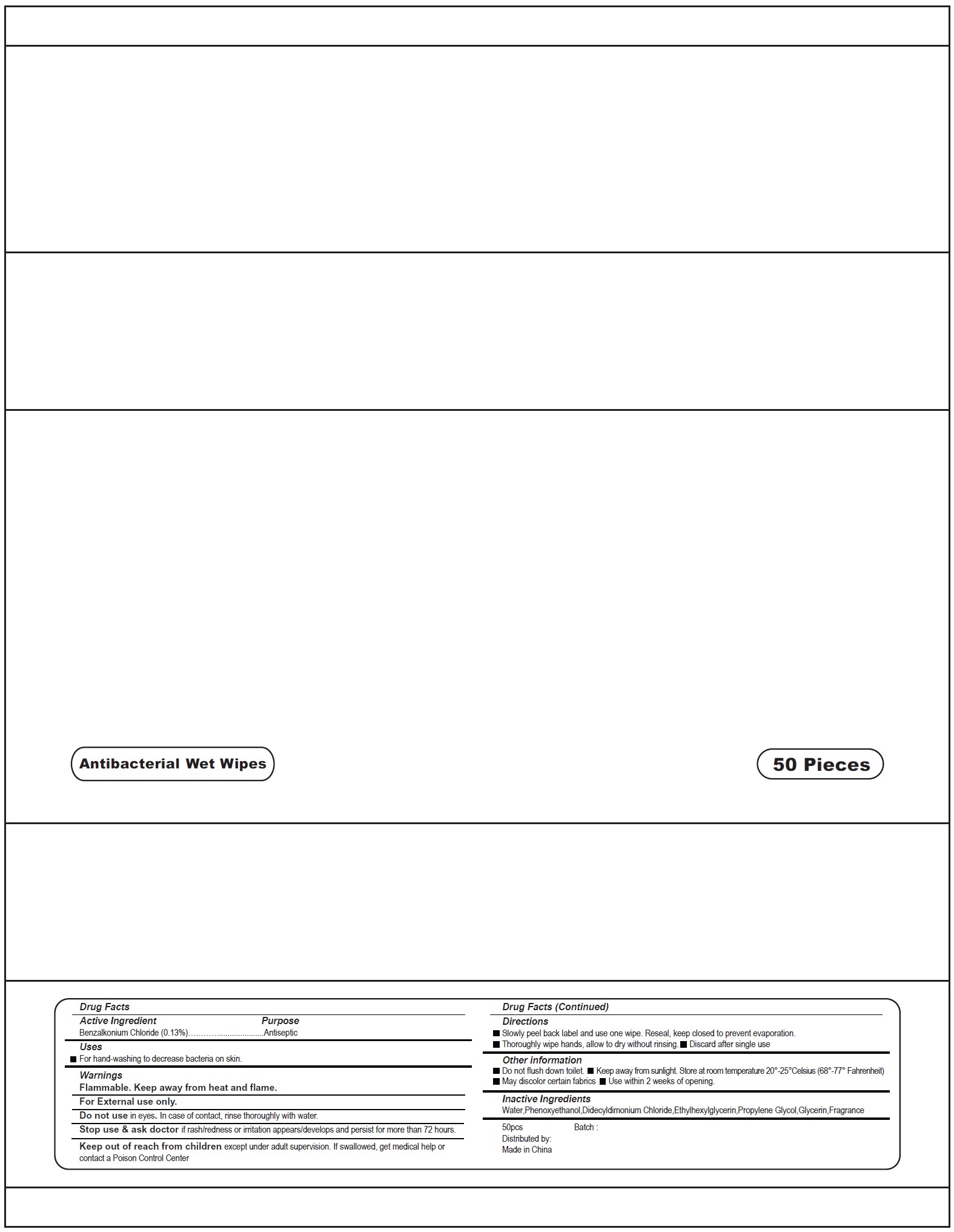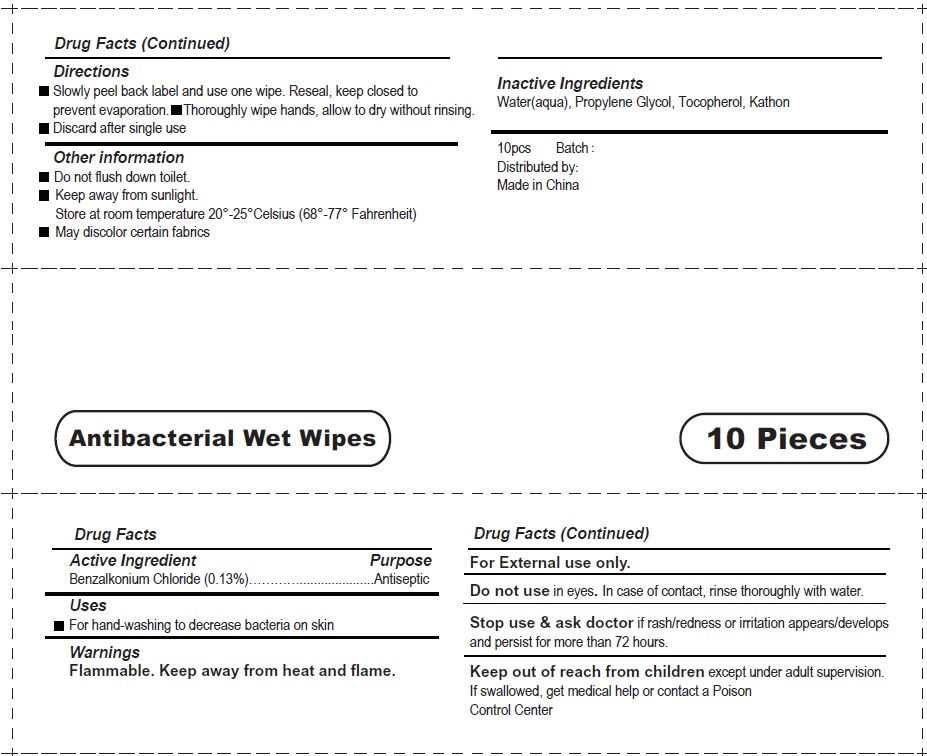 DRUG LABEL: Antibacterial Wet Wipes
NDC: 70412-500 | Form: CLOTH
Manufacturer: Zhejiang Ayan Biotech Co.,Ltd.
Category: otc | Type: HUMAN OTC DRUG LABEL
Date: 20231106

ACTIVE INGREDIENTS: BENZALKONIUM CHLORIDE 0.13 g/100 g
INACTIVE INGREDIENTS: WATER; PROPYLENE GLYCOL; TOCOPHEROL; OCTHILINONE

Antibacterial Wet Wipes

Active Ingredient

Benzalkonium Chloride (0.13%)

Purpose

Antiseptic

Uses

For hand-washing to decrease bacteria on skin

Warnings

Flammable. Keep away from heat and flame.

For External use only.

Do not use

in eyes. In case of contact, rinse thoroughly with water.

Stop use & ask doctor

if rash/redness or irritation appears/develops and persist for more than 72 hours.

Keep out of reach from children

except under adult supervision. If swallowed, get medical help or contact a Poison Control Center

Directions

- Slowly peel back label and use one wipe. Reseal, keep closed to prevent evaporation.
- Thoroughly wipe hands, allow to dry without rinsing.
- Discard after single use

Other information

- Do not flush down toilet.
- Keep away from sunlight. Store at room temperature 20°-25°Celsius (68°-77° Fahrenheit)
- May discolor certain fabrics

Inactive Ingredients

Water(aqua), Propylene Glycol, Tocopherol, Kathon